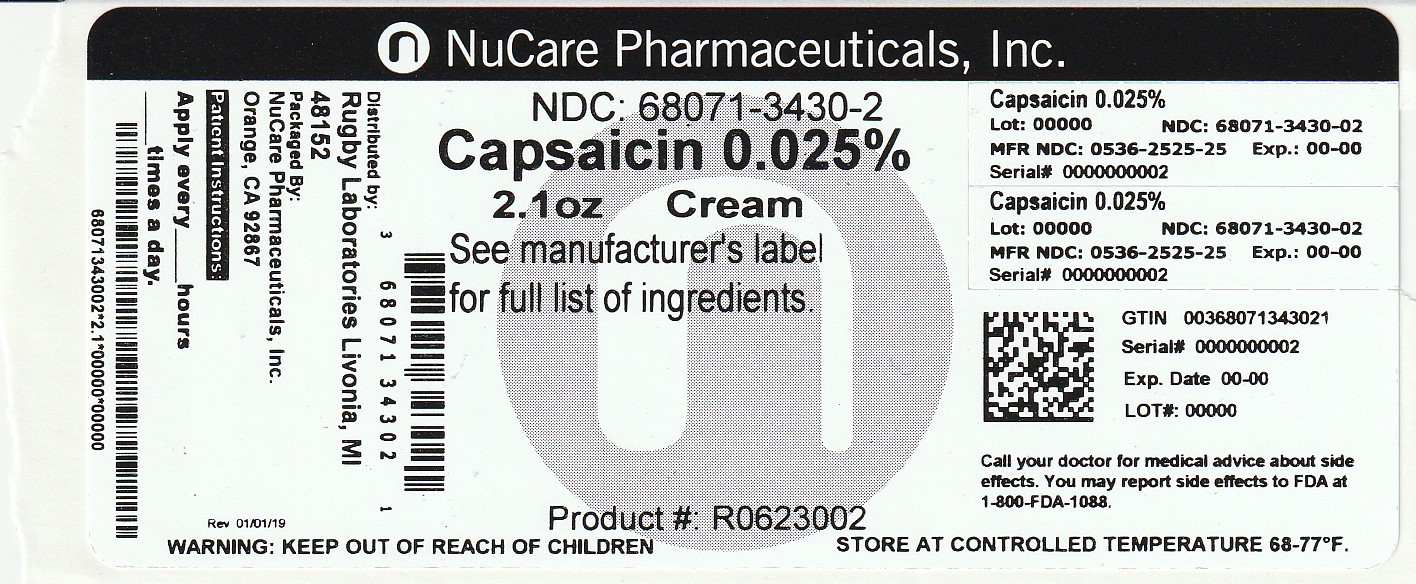 DRUG LABEL: Capsaicin
NDC: 68071-3430 | Form: CREAM
Manufacturer: NuCare Pharmaceuticals,Inc.
Category: otc | Type: HUMAN OTC DRUG LABEL
Date: 20250204

ACTIVE INGREDIENTS: CAPSAICIN 0.25 mg/1 g
INACTIVE INGREDIENTS: CARBOMER COPOLYMER TYPE A (ALLYL PENTAERYTHRITOL CROSSLINKED); CETYL ACETATE; METHYLPARABEN; PPG-20 METHYL GLUCOSE ETHER DISTEARATE; PROPYLENE GLYCOL; PROPYLPARABEN; STEARETH-100; STEARIC ACID; STEARYL ALCOHOL; TROLAMINE; WATER

Rugby® Capsaicin Cream
External Analgesic

Drug Facts

Active ingredient

Capsaicin 0.025%

Purpose

External analgesic

Uses

temporarily relieves minor aches and pains of muscles and joints due to:

- simple backache
- arthritis
- strains
- sprains

Warnings

For external use only

Read all warnings and directions before use. Test first on small area of skin.

Do not use

- on wounds or damaged skin
- if you are allergic to capsicum or chili peppers

When using this product

- you may experience a burning sensation. The intensity of this reaction varies among individuals and may be severe. With regular use, this sensation generally disappears after several days.
- avoid contact with the eyes, lips, nose and mucous membranes
- do not tightly wrap or bandage the treated area
- do not apply heat to the treated area immediately before or after use

Stop use and ask a doctor if

- condition worsens or does not improve after regular use
- severe burning persists or blistering occurs

Keep out of reach of children. If swallowed, get medical help or contact a Poison Control Center immediately.

Directions

Adults and children 18 years of age and older:

- apply a thin film of cream to affected area and gently rub in until fully absorbed
- unless treating hands, wash hands thoroughly with soap and water immediately after application
- for best results, apply 3 to 4 times daily.

Children under 18 years: ask a doctor

Other information

store at room temperature 15° - 30°C (59° - 86°F)

Inactive ingredients

acrylates/C10-30 alkyl acrylate crosspolymer, cetyl acetate, methylparaben, PPG-20 methyl glucose ether distearate, propylene glycol, propylparaben, stearate-100, stearic acid, stearyl alcohol, triethanolamine, water

Questions or comments?

Call 1-800-645-2158 9 am - 5 pm ET, Monday - Friday

Mfd for:
Rugby Laboratories, Inc.
Duluth, Georgia 30097